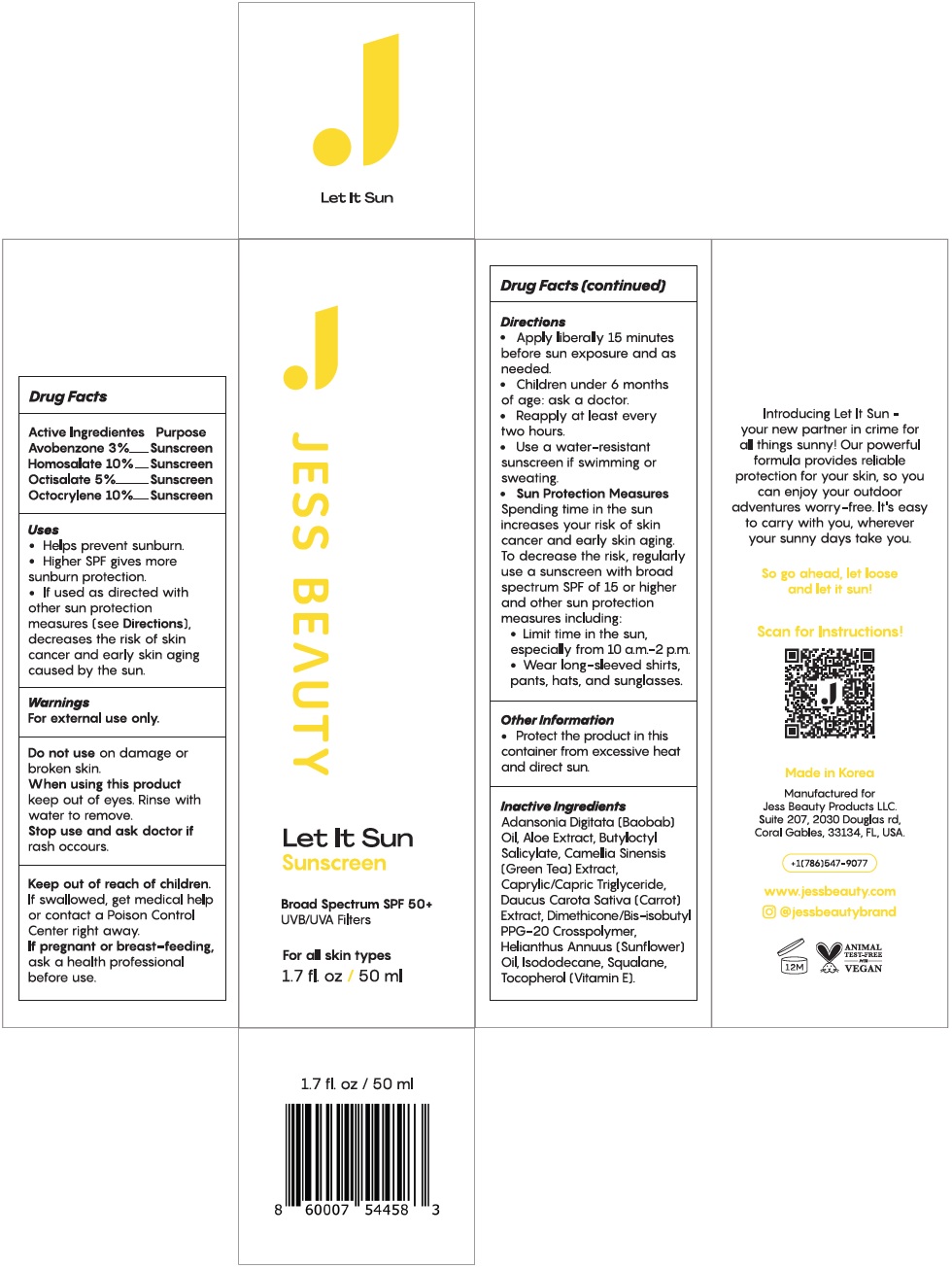 DRUG LABEL: JESS BEAUTY Let It Sun Sunscreen SPF-50
NDC: 83542-410 | Form: LOTION
Manufacturer: JESS BEAUTY PRODUCTS LLC
Category: otc | Type: HUMAN OTC DRUG LABEL
Date: 20231106

ACTIVE INGREDIENTS: AVOBENZONE 30 mg/1 mL; HOMOSALATE 100 mg/1 mL; OCTISALATE 50 mg/1 mL; OCTOCRYLENE 100 mg/1 mL
INACTIVE INGREDIENTS: ALOE; BUTYLOCTYL SALICYLATE; GREEN TEA LEAF; MEDIUM-CHAIN TRIGLYCERIDES; CARROT; DIMETHICONE/BIS-ISOBUTYL PPG-20 CROSSPOLYMER; HELIANTHUS ANNUUS FLOWERING TOP; ISODODECANE; SQUALANE; TOCOPHEROL

JESS BEAUTY Let It Sun Sunscreen SPF-50

Active Ingredientes

Avobenzone 3%

Homosalate 10%

Octisalate 5%

Octocrylene 10%

Purpose

Sunscreen

Uses

- Helps prevent sunburn.
- Higher SPF gives more sunburn protection.
- If used as directed with other sun protection measures (see Directions), decreases the risk of skin cancer and early skin aging caused by the sun

Warnings

For external use only.

Do not use

on damaged or broken skin.

When using this product

keep out of eyes. Rinse with water to remove.

Stop use and ask doctor if

rash occours.

Keep out of reach of children.

If swallowed, get medical help or contact a Poison Control Center right away.

If pregnant or breast-feeding,

ask a health professional before use.

Directions

- Apply liberally 15 minutes before sun exposure and as needed.
- Children under 6 months of age: ask a doctor.
- Reapply at least every two hours.
- Use a water-resistant sunscreen if swimming or sweating.
- Spending time in the sun increases your risk of skin cancer and early skin aging. To decrease the risk, regularly use a sunscreen with broad spectrum SPF of 15 or higher and other sun protection measures including: Sun Protection Measures
- Limit time in the sun, especially from 10 a.m.-2 p.m.
- Wear long-sleeved shirts, pants, hats, and sunglasses.

Other Information

- Protect the product in this container from excessive heat and direct sun.

Inactive Ingredients

Adansonia Digitata (Baobab) Oil, Aloe Extract, Butyloctyl Salicylate, Camellia Sinensis (Green Tea) Extract, Caprylic/Capric Triglyceride, Daucus Carota Sativa (Carrot) Extract, Dimethicone/Bis-isobutyl PPG-20 Crosspolymer, Helianthus Annuus (Sunflower) Oil, Isododecane, Squalane, Tocopherol (Vitamin E).